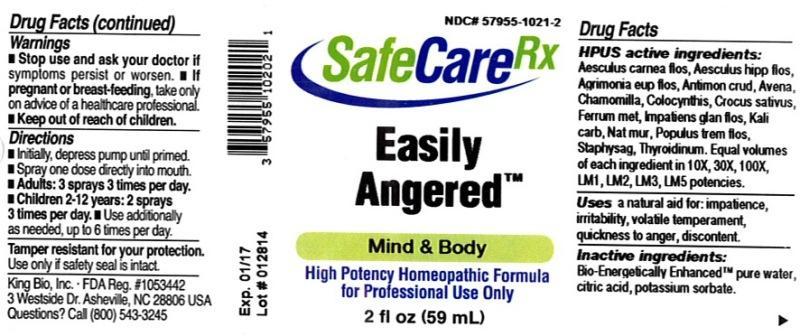 DRUG LABEL: Easily Angered
NDC: 57955-1021 | Form: LIQUID
Manufacturer: King Bio Inc.
Category: homeopathic | Type: HUMAN OTC DRUG LABEL
Date: 20140402

ACTIVE INGREDIENTS: AESCULUS CARNEA FLOWER 10 [hp_X]/59 mL; AESCULUS HIPPOCASTANUM FLOWER 10 [hp_X]/59 mL; AGRIMONIA EUPATORIA FLOWER 10 [hp_X]/59 mL; ANTIMONY TRISULFIDE 10 [hp_X]/59 mL; AVENA SATIVA FLOWERING TOP 10 [hp_X]/59 mL; MATRICARIA RECUTITA 10 [hp_X]/59 mL; CITRULLUS COLOCYNTHIS FRUIT PULP 10 [hp_X]/59 mL; SAFFRON 10 [hp_X]/59 mL; IRON 10 [hp_X]/59 mL; IMPATIENS GLANDULIFERA FLOWER 10 [hp_X]/59 mL; POTASSIUM CARBONATE 10 [hp_X]/59 mL; SODIUM CHLORIDE 10 [hp_X]/59 mL; POPULUS TREMULA FLOWERING TOP 10 [hp_X]/59 mL; DELPHINIUM STAPHISAGRIA SEED 10 [hp_X]/59 mL; THYROID, UNSPECIFIED 10 [hp_X]/59 mL
INACTIVE INGREDIENTS: WATER; CITRIC ACID MONOHYDRATE; POTASSIUM SORBATE

Easily Angered™

ACTIVE INGREDIENT

Drug Facts__________________________________________________________________________________________________________

HPUS activeingredients: Aesculus carnea, flos, Aesculus hippocastanum, flos, Agrimonia eupatoria, flos, Antimonium crudum, Avena sativa, Chamomilla, Colocynthis, Crocus sativus, Ferrum metallicum, Impatiens glandulifera, flos, Kali carbonicum, Natrum muriaticum, Populus tremula, flos, Staphysagria, Thyroidinum. Equal volumes of each ingredient in 10X, 30X, 100X, LM1, LM2, LM3, LM5 potencies.

INDICATIONS AND USAGE

Uses a natural aid for: impatience, irritability, volatile temperament, quickness to anger, discontent.

Inactive Ingredients:

Bio-Energetically Enhanced™ pure water, citric acid and potassium sorbate.

Warnings

- Stop use and ask your doctor if symptoms persist or worsen.
- If pregnant or breast-feeding, take only on advice of a healthcare professional.

- Keep out of reach of children

Directions

- Initially, depress pump until primed.
- Spray one dose directly into mouth.
- Adults: 3 sprays 3 times per day.
- Children 2-12 years: 2 sprays 3 times per day.
- Use additonally as needed, up to 6 times per day.

OTHER SAFETY INFORMATION

Tamper resistant for your protection. Use only if safety seal is intact.

PURPOSE

Uses a natural aid for:

- impatience
- irritability
- volatile temperament
- quickness to anger
- discontent